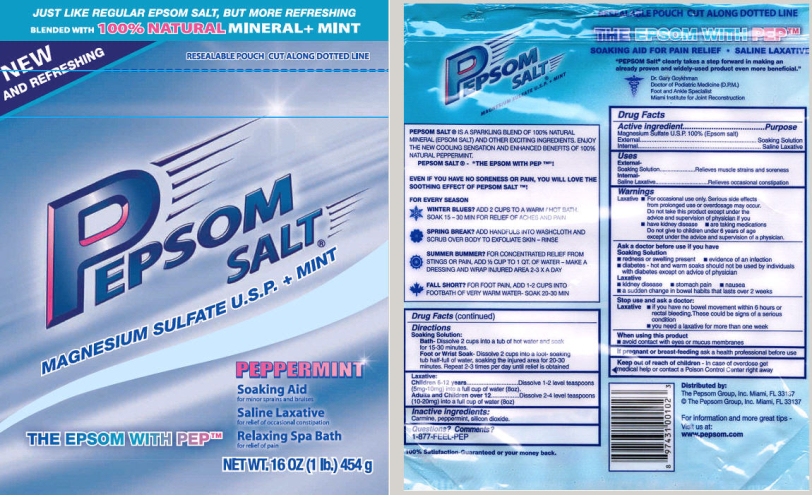 DRUG LABEL: PEPSOM SALT PEPPERMINT 
NDC: 51619-500 | Form: FOR SOLUTION
Manufacturer: The Pepsom Group, Inc.
Category: otc | Type: HUMAN OTC DRUG LABEL
Date: 20100527

ACTIVE INGREDIENTS: Magnesium Sulfate, Unspecified 1 kg/1 kg
INACTIVE INGREDIENTS: Peppermint; Silicon Dioxide

Pepsom Salt Magnesium Sulfate U.S.P. + Mint
Drug Facts

Active Ingredient

Magnesium Sulfate U.S.P. 100% (Epsom salt)

Purpose

External...................Soaking Solution
Internal.......................Saline Laxative

Uses

External-
Soaking Solution.............Relieves muscle strains and soreness
Internal-
Saline Laxative........................Relieves occasional constipation

Warnings

Laxative

- For occasional use only. Serious side effects from prolonged use or overdosage may occur. Do not take this product except under the advice and supervision of physician if you
  - have kidney disease
  - are taking medications
  Do not give to children under 6 years of age except under the advice and supervision of a physician.

Ask a doctor before use if you have

Soaking Solution

- redness or swelling present
- evidence of an infection
- diabetes - hot and warm soaks should not be used by individuals with diabetes except on advice of physician

Laxative

- kidney disease
- stomach pain
- nausea
- a sudden change in bowel habits that lasts over 2 weeks

Stop use and ask a doctor:

Laxative

- if you have no bowel movement within 6 hours or rectal bleeding. These could be signs of a serious condition
- you need a laxative for more than one week

When using this product

- avoid contact with eyes or mucus membranes

PREGNANCY OR BREAST FEEDING

If pregnant or breast-feeding ask a health professional before use

Keep out of reach of children -

In case of overdose get medical help or contact a Poison Control Center right away

Directions

Soaking Solution:

Bath - Dissolve 2 cups into a tub of hot water and soak for 15-30 minutes.
Foot or Wrist Soak - Dissolve 2 cups into a foot-soaking tub half-full of water, soaking the injured area for 20-30 minutes.
Repeat 2-3 times per day until relief is obtained

Laxative:

Children 6-12 years.........................Dissolve 1-2 level teaspoons
(5mg-10mg) into a full cup of water (8oz)
Adults and Children over 12.........Dissolve 2-4 level teaspoons
(10mg-20mg) into a full cup of water (8oz)

Inactive ingredients:

Carmine, peppermint, silicon dioxide.

Questions? Comments?

1-877-FEEL-PEP

Principal Display Panel

JUST LIKE REGULAR EPSOM SALT, BUT MORE REFRESHING

BLENDED WITH 100% NATURAL MINERAL+ MINT

NEW AND REFRESHING

RESEALABLE POUCH CUT ALONG DOTTED LINE

PEPSOM SALT®

MAGNESIUM SULFATE U.S.P. + MINT

PEPPERMINT

Soaking Aid
for minor sprains and bruises

Saline Laxative
for relief of occasional constipation

Relaxing Spa Bath
for relief of pain

THE EPSOM WITH PEP™

NET WT. 16 OZ (1 lb.) 454 g

RESEALABLE POUCH CUT ALONG DOTTED LINE

THE EPSOM WITH PEP™

SOAKING AID FOR PAIN RELIEF • SALINE LAXATIVE

"PEPSOM Salt® clearly takes a step forward in making an already proven and widely-used product even more beneficial."
Dr. Gary Goykhman
Doctor of Podiatric Medicine (D.P.M.)
Foot and Ankle Specialist
Miami Institute for Joint Reconstruction

PEPSOM SALT® IS A SPARKLING BLEND OF 100% NATURAL MINERAL (EPSOM SALT) AND OTHER EXCITING INGREDIENTS. ENJOY THE NEW COOLING SENSATION AND ENHANCED BENEFITS OF 100% NATURAL PEPPERMINT.

PEPSOM SALT® - "THE EPSOM WITH PEP ™"!

EVEN IF YOU HAVE NO SORENESS OR PAIN, YOU WILL LOVE THE SOOTHING EFFECT OF PEPSOM SALT ™!

FOR EVERY SEASON

WINTER BLUES? ADD 2 CUPS TO A WARM/HOT BATH. SOAK 15-30 MIN FOR RELIEF OF ACHES AND PAINS

SPRING BREAK? ADD HANDFULS INTO WASHCLOTH AND SCRUB OVER BODY TO EXFOLIATE SKIN - RINSE

SUMMER BUMMER? FOR CONCENTRATED RELIEF FROM STINGS OR PAIN, ADD ½ CUP TO 1 QT. OF WATER - MAKE A DRESSING AND WRAP INJURED AREA 2-3 X A DAY

FALL SHORT? FOR FOOT PAIN, ADD 1-2 CUPS INTO FOOTBATH OF VERY WARM WATER - SOAK 20-30 MIN

100% Satisfaction-Guaranteed or your money back.

Distributed by:
The Pepsom Group, Inc. Miami, FL 33137
© The Pepsom Group, Inc. Miami, FL 33137

For information and more great tips -
Visit us at:
www.pepsom.com